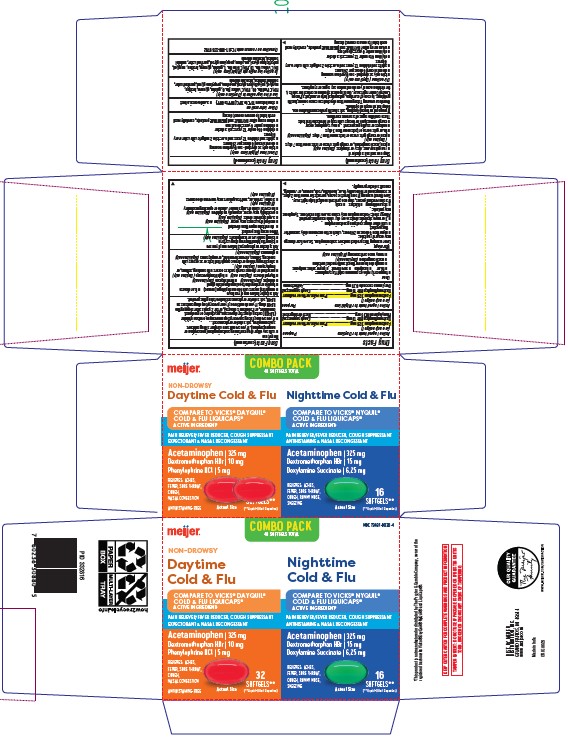 DRUG LABEL: Cold and Flu Non Drowsy Daytime and Nighttime
NDC: 79481-0030 | Form: KIT | Route: ORAL
Manufacturer: Meijer, Inc.
Category: otc | Type: HUMAN OTC DRUG LABEL
Date: 20241220

ACTIVE INGREDIENTS: ACETAMINOPHEN 325 mg/1 1; DEXTROMETHORPHAN HYDROBROMIDE 10 mg/1 1; PHENYLEPHRINE HYDROCHLORIDE 5 mg/1 1; ACETAMINOPHEN 325 mg/1 1; DEXTROMETHORPHAN HYDROBROMIDE 10 mg/1 1; DOXYLAMINE SUCCINATE 6.25 mg/1 1
INACTIVE INGREDIENTS: FD&C RED NO. 40; FD&C YELLOW NO. 6; GELATIN; GLYCERIN; LECITHIN, SOYBEAN; MEDIUM-CHAIN TRIGLYCERIDES; POLYETHYLENE GLYCOL 400; POVIDONE; PROPYLENE GLYCOL; SORBITOL; TITANIUM DIOXIDE; D&C YELLOW NO. 10; FD&C BLUE NO. 1; GELATIN; GLYCERIN; LECITHIN, SOYBEAN; MEDIUM-CHAIN TRIGLYCERIDES; POLYETHYLENE GLYCOL 400; POVIDONE; PROPYLENE GLYCOL; SORBITOL; SORBITAN; TITANIUM DIOXIDE

Cold and Flu Non Drowsy Daytime and Nighttime

Active ingredients (in each softgel)

COLD & FLU NON-DROWSY DAY RELIEF

Acetaminophen 325 mg
Dextromethorphan hydrobromide 10 mg
Phenylephrine hydrochloride 5 mg

COLD & FLU NIGHT RELIEF

Acetaminophen 325 mg
Dextromethorphan hydrobromide 10 mg

Doxylamine succinate 6.25 mg

Purposes

COLD & FLU NON DROWSY DAY RELIEF

Pain reliever/fever reducer

Cough suppressant

Nasal decongestant

COLD & FLU NIGHT RELIEF

Pain reliever/fever reducer

Cough suppressant

Antihistamine

Uses

temporarily relieves common cold/flu symptoms:

- fever
- headache
- minor aches and pain
- cough due to minor throat and bronchial iffitation
- sore throat
- nasal congestion (Daytime only)
- runny nose and sneezing (Nighttime only)

Warnings

Liver warning This product contains acetaminophen. Severe liver damage may occur if you take: ● more than 4 doses in 24 hours, which is the
maximum daily amount for this product ● with other drugs containing acetaminophen ● 3 or more alcoholic drinks every day while using this product

Allergy alert: Acetaminophen may cause severe skin reactions.
Symptoms may include: ● skin reddening ● blisters ● rash
If a skin reaction occurs, stop use and seek medical help right away.

Sore throat warning If sore throat is severe, persists for more than 2 days, is accompanied or followed by fever, headache, rash, nausea, or vomiting, consult a doctor promptly.

Do not use

● with any other drug containing acetaminophen (prescription or nonprescription). If you are not sure whether a drug contains
acetaminophen, ask a doctor or pharmacist.
● if you are now taking a prescription monoamine oxidase inhibitor (MAOI) (certain drugs for depression, psychiatric or emotional conditions, or Parkinson's disease), or for 2 weeks after stopping the MAOI drug. If you do not know if your prescription drug contains an MAOI, ask a doctor or pharmacist before taking this product.● if you have ever had an allergic reaction to this product or any of its ingredients● to make a child sleepy (Nighttime only)

Ask a doctor before use if you have

● cough that occurs with too much phlegm (mucus) ● liver disease
● trouble urinating due to enlarged prostate gland
● diabetes (Daytime only) ● heart disease (Daytime only)
● thyroid disease (Daytime only) ● high blood pressure (Daytime only)
● persistent or chronic cough such as occurs with smoking, asthma, or emphysema (Daytime only)
● a breathing problem or chronic cough that lasts or as occurs with smoking, asthma, chronic bronchitis, or emphysema (Nighttime only)
● glaucoma (Nighttime only)

Ask a doctor or pharmacist before use if you are

● taking the blood thinning drug warfarin
● taking sedatives or tranquilizers (Nighttime only)

When using this product

● do not take more than directed
● marked drowsiness may occur (Nighttime only)
● avoid alcoholic drinks (Nighttime only)
● excitability may occur, especially in children (Nighttime only)
● be careful when driving a motor vehicle or operating machinery (Nighttime only)
● alcohol, sedatives, and tranquilizers may increase drowsiness (Nighttime only)

Stop use and ask a doctor if

● you get nervous, dizzy or sleepless (Daytime only)
● pain, nasal congestion, or cough gets worse or lasts more than 7 days (Daytime only)
● pain or cough gets worse or lasts more than 7 days (Nighttime only)
● fever gets worse or lasts more than 3 days
● redness or swelling is present
● new symptoms occur
● cough comes back or occurs with rash or headache that lasts
These could be signs of a serious condition.

PREGNANCY OR BREAST FEEDING

If pregnant or breast-feeding, ask a health professional before use.

Keep out of reach of children.

OVERDOSAGE

Overdose warning Taking more than directed can cause serious health problems. In case of overdose, get medical help or contact a Poison Control Center right away. Quick medical attention is critical for adults & for children even if you do not notice any signs or symptoms.

Directions

● when using other DAYTIME and NIGHTTIME products, carefully read each
label to ensure correct dosing

Directions (Daytime only)
● take only as directed - see Overdose warning
● do not exceed 4 doses per 24 hours

adults & children 12 years & over | take 2 softgels with water every 4 hours
children 4 to under 12 years | ask a doctor
children under 4 years of age | do not use

● when using other DAYTIME and NIGHTTIME products, carefully read each label to ensure correct dosing
Directions (Nighttime only)

● take only as directed - see Overdose warning
● do not exceed 4 doses per 24 hours

adults & children 12 years & over | take 2 softgels with water every 6 hours
children 4 to under 12 years | ask a doctor
children under 4 years of age | do not use

Other information

- store at room temperature.

Inactive ingredients

DAY RELIEF

FD&C Red# 40, FD&C Yellow# 6, gelatin, glycerin, polyethylene glycol, myglyol, lecithin, povidone, propylene glycol, purified water, sorbitol sorbitan, titanium dioxide

NIGHT RELIEF

D&C Yellow# 10, FD&C Blue# 1, gelatin, glycerin, myglyol, lecithin, polyethylene glycol, povidone, propylene glycol, purified water, sorbitol sorbitan, polysorb, sorbitol sorbitan, titanium dioxide

Questions or comments?

1-888-333-9792